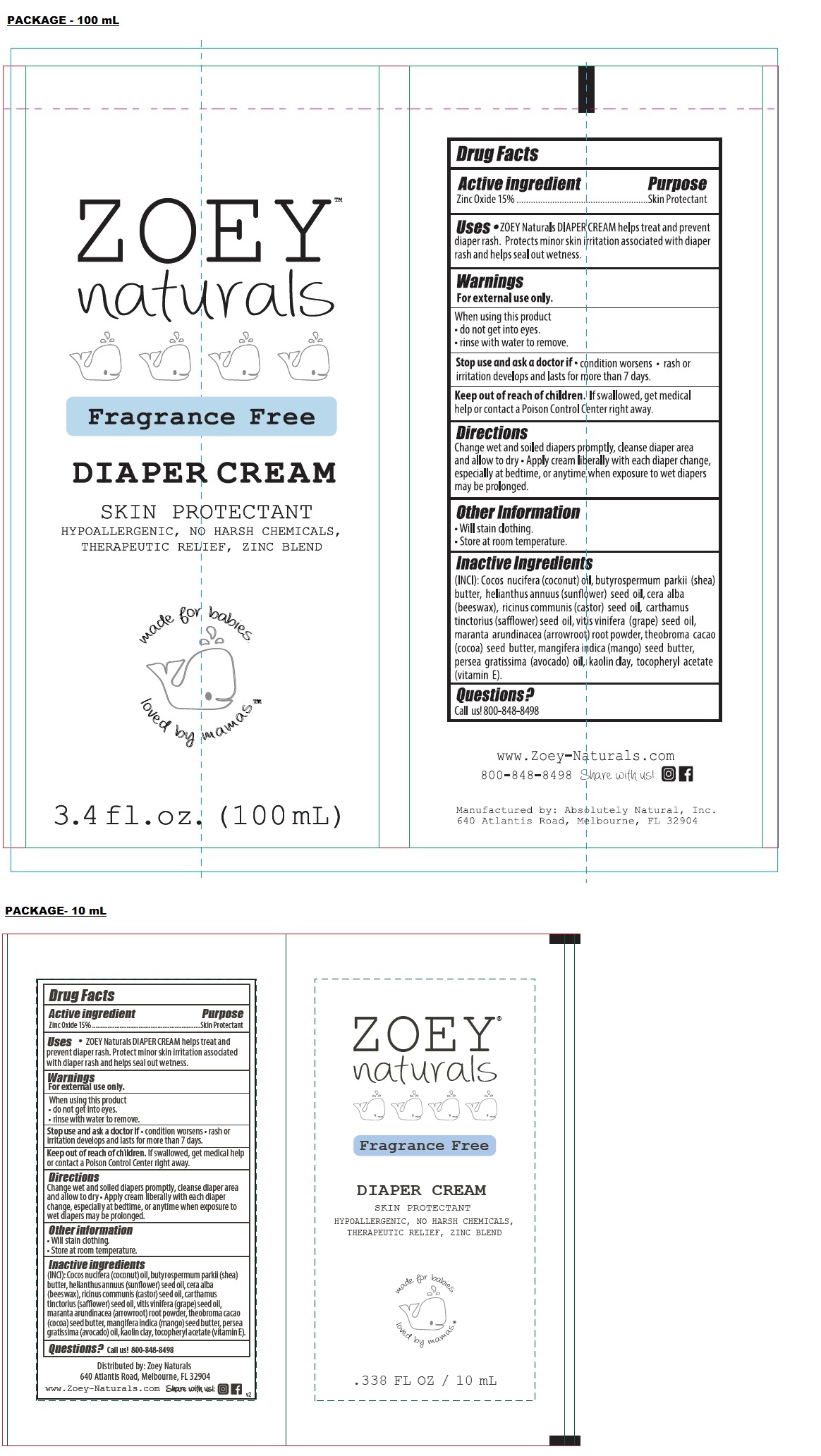 DRUG LABEL: ZOEY NATURALS DIAPER Cream
NDC: 70793-010 | Form: CREAM
Manufacturer: Absolutely Natural
Category: otc | Type: HUMAN OTC DRUG LABEL
Date: 20240625

ACTIVE INGREDIENTS: ZINC OXIDE 15 g/100 mL
INACTIVE INGREDIENTS: COCONUT OIL; SHEA BUTTER; SUNFLOWER OIL; WHITE WAX; CASTOR OIL; SAFFLOWER OIL; GRAPE SEED OIL; MARANTA ARUNDINACEA ROOT; COCOA BUTTER; MANGIFERA INDICA SEED BUTTER; AVOCADO OIL; KAOLIN; .ALPHA.-TOCOPHEROL ACETATE

ZOEY NATURALS DIAPER CREAM

Active ingredient

Zinc Oxide 15%

Purpose

Skin Protectant

Uses

• ZOEY Naturals DIAPER CREAM helps treat and prevent diaper rash. Protect minor skin irritation associated with diaper rash and helps seal out wetness.

Warnings

For external use only.

When using this product

• do not get into eyes.

• rinse with water to remove.

Stop use and ask doctor if • condition worsens • rash or irritation develops and lasts for more than 7 days.

Keep out of reach of children. If swallowed, get medical help or contact a Poison Control Center right away.

Directions

Change wet and soiled diapers promptly, cleanse diaper area and allow to dry • Apply cream liberally with each diaper change, especially at bedtime, or anytime when exposure to wet diapers may be prolonged.

Other information

• Will stain clothing

• Store at room temperature

Inactive ingredients

(INCI): Cocoa nucifera (coconut) oil, butyrospermum parkii (shea) butter, helianthus annuus (sunflower) seed oil, cera alba (beeswax), ricinus communis (castor) seed oil, carthamus tinctorius (safflower) seed oil, vitis vinifera (grape) seed oil, maranta arundinacea (arrowroot) root powder, theobroma cacao (cocoa) seed butter, mangifera indica (mango) seed butter, persea gratissima (avocado) oil, kaolin clay, tocopheryl acetate (vitamin E).

Questions?

Call us! 800-848-8498

Fragrance Free

SKIN PROTECTANT

HYPOALLERGENIC, NO HARSH CHEMICALS, THERAPEUTIC RELIEF, ZINC BLEND

made for babies

loved by mamas

www.Zoey-Naturals.com

Manufactured by: Absolutely Natural, Inc.

640 Atlantis Road, Melbourne, FL 32904

Distributed by: Zoey Naturals
640 Atlantis Road, Melbourne, FL 32904